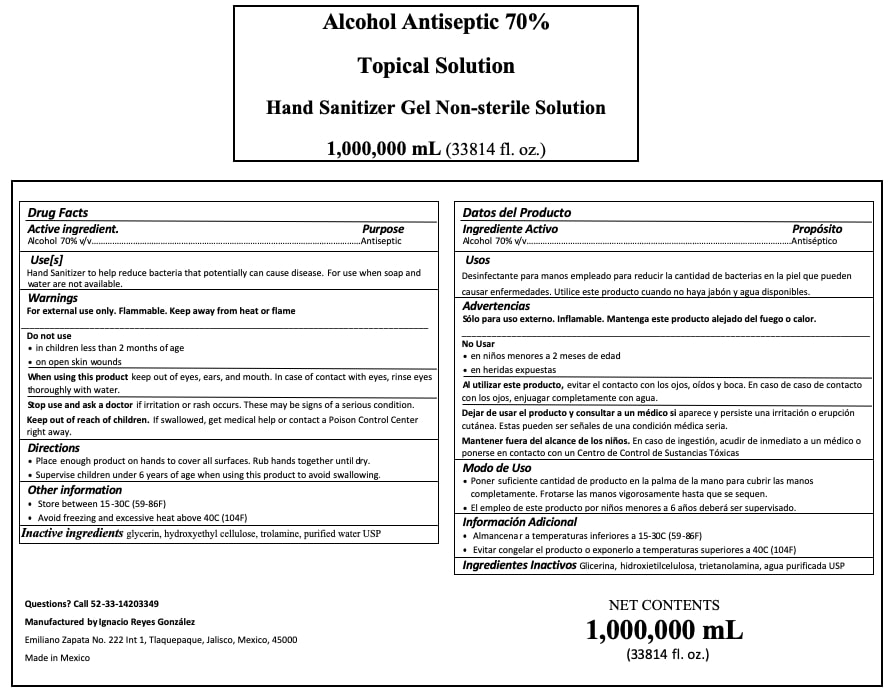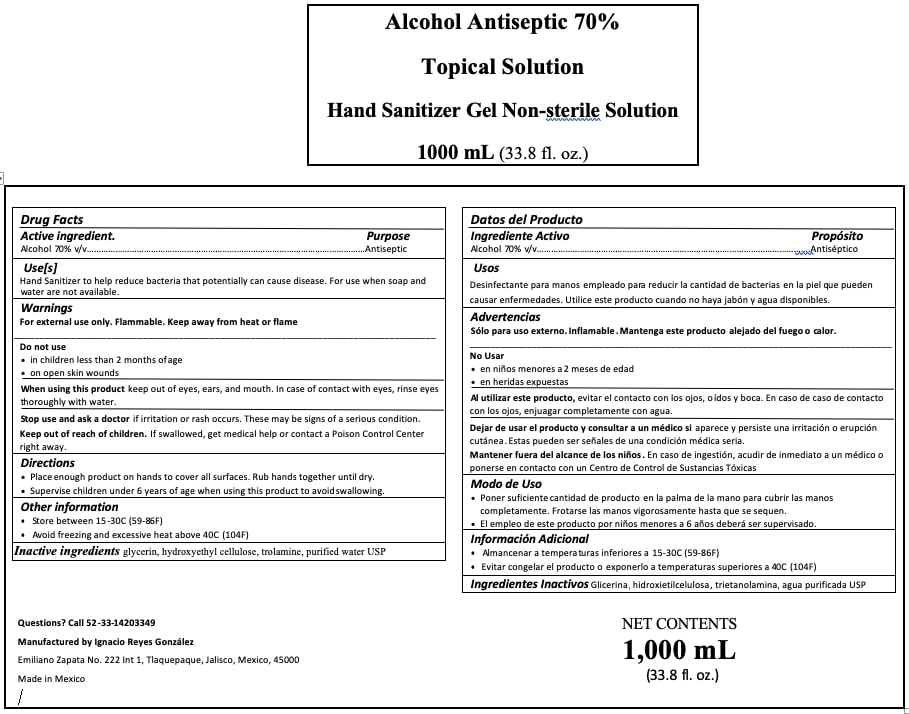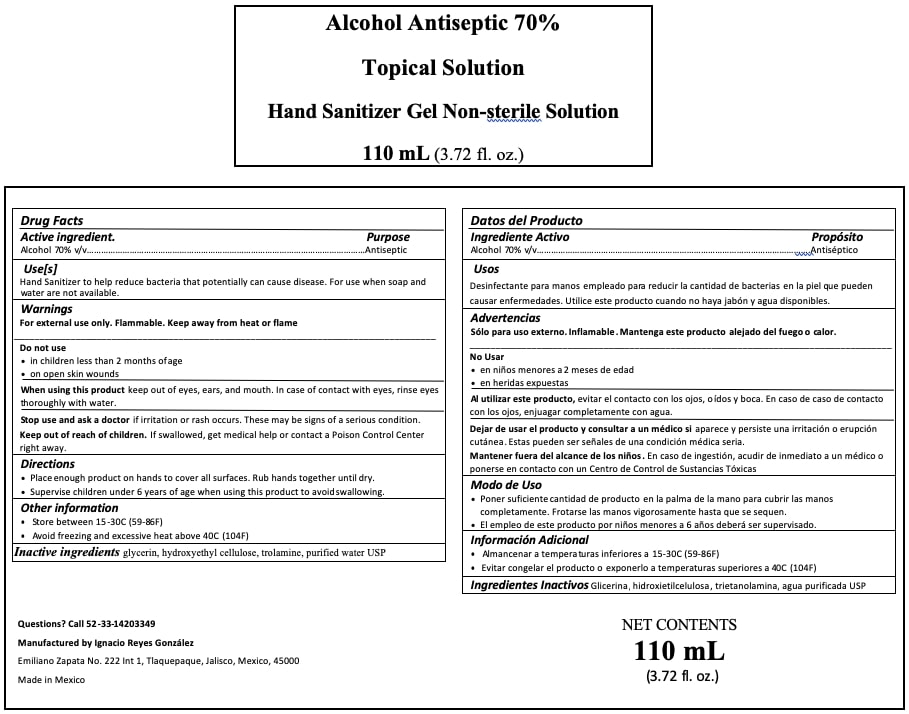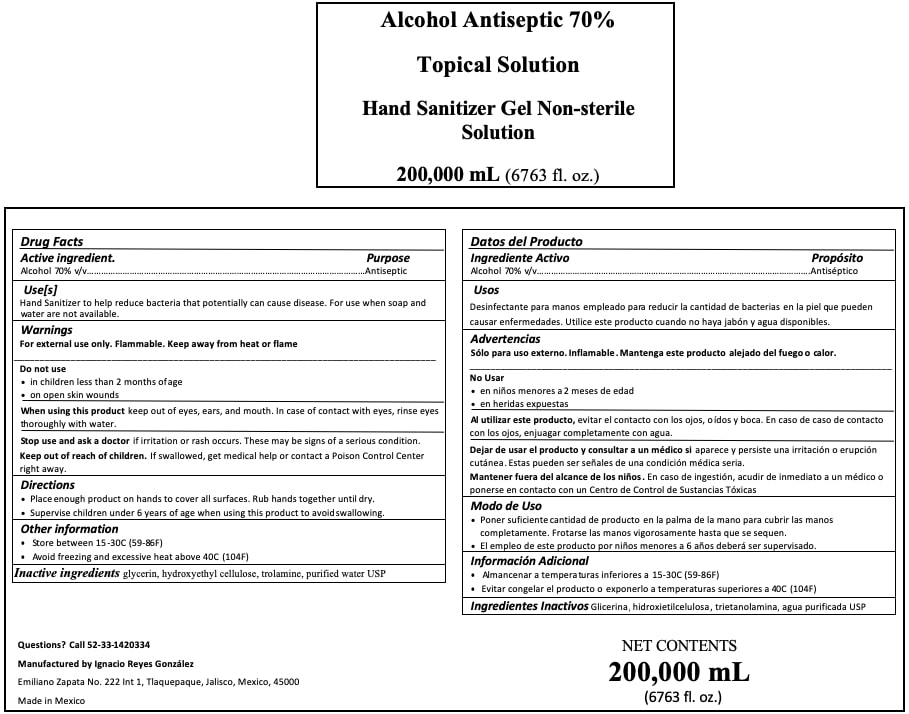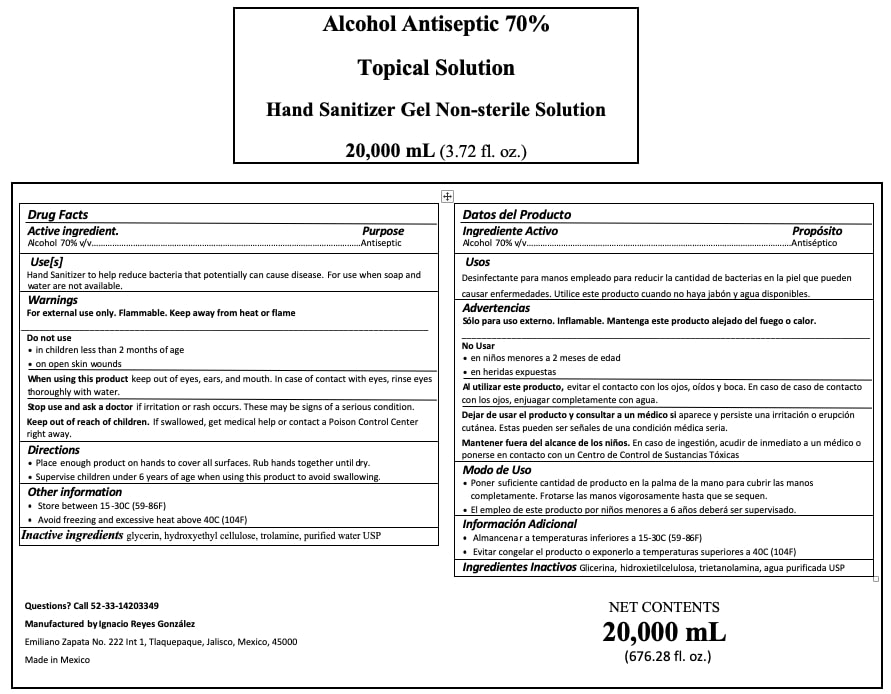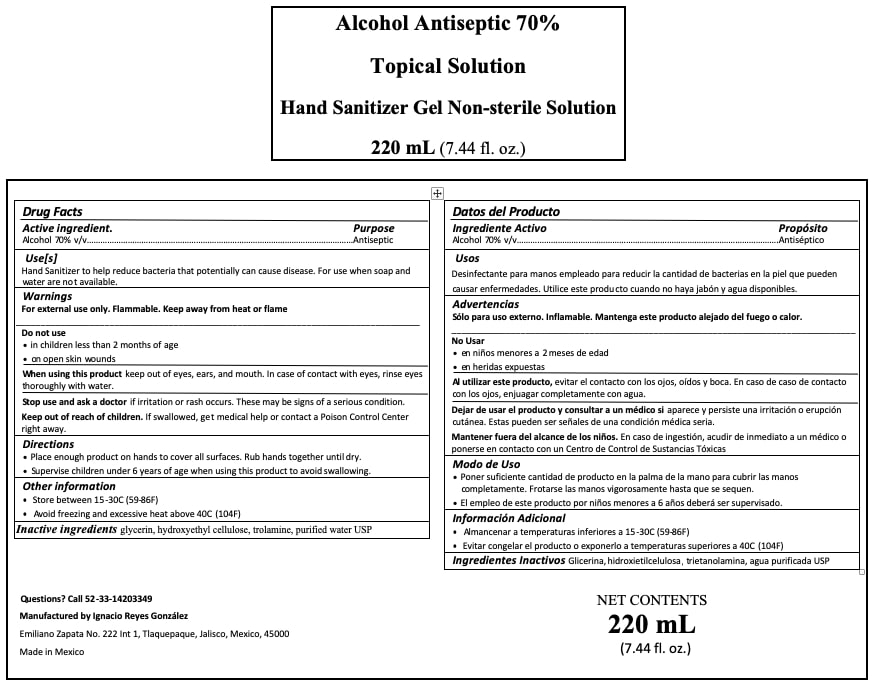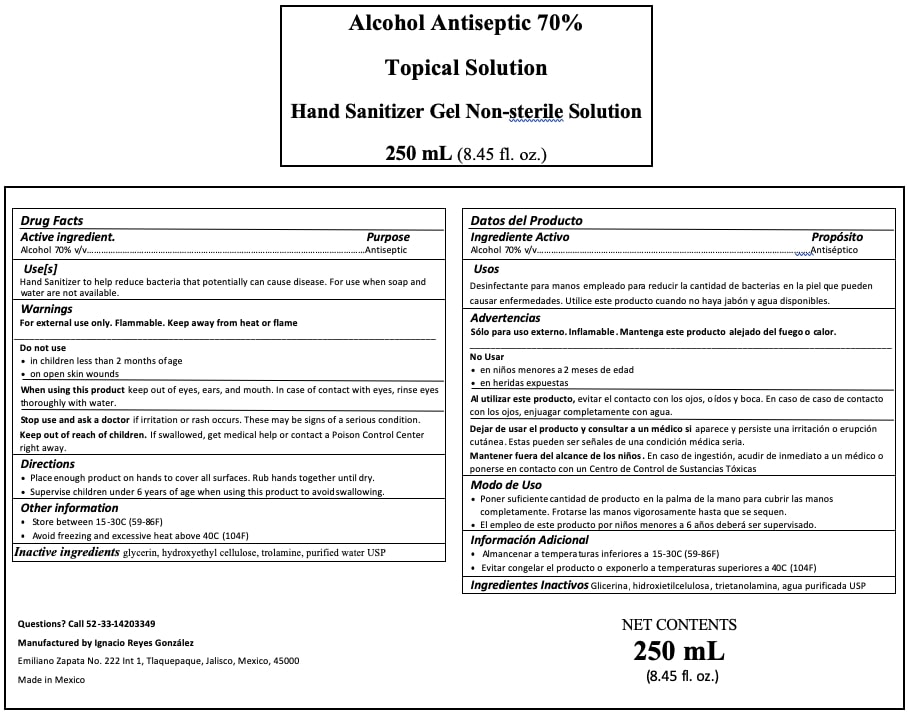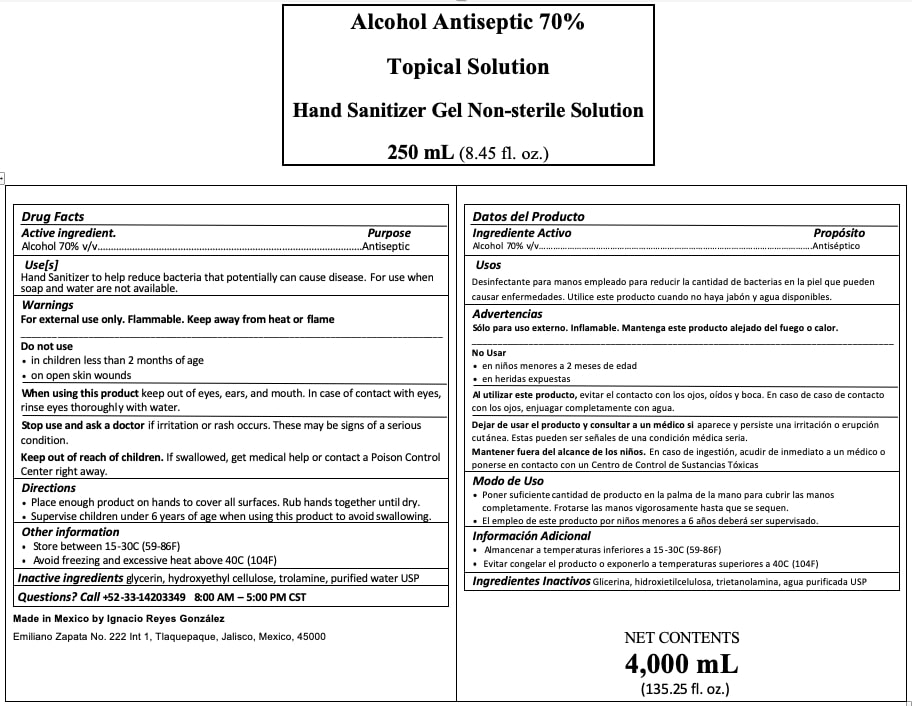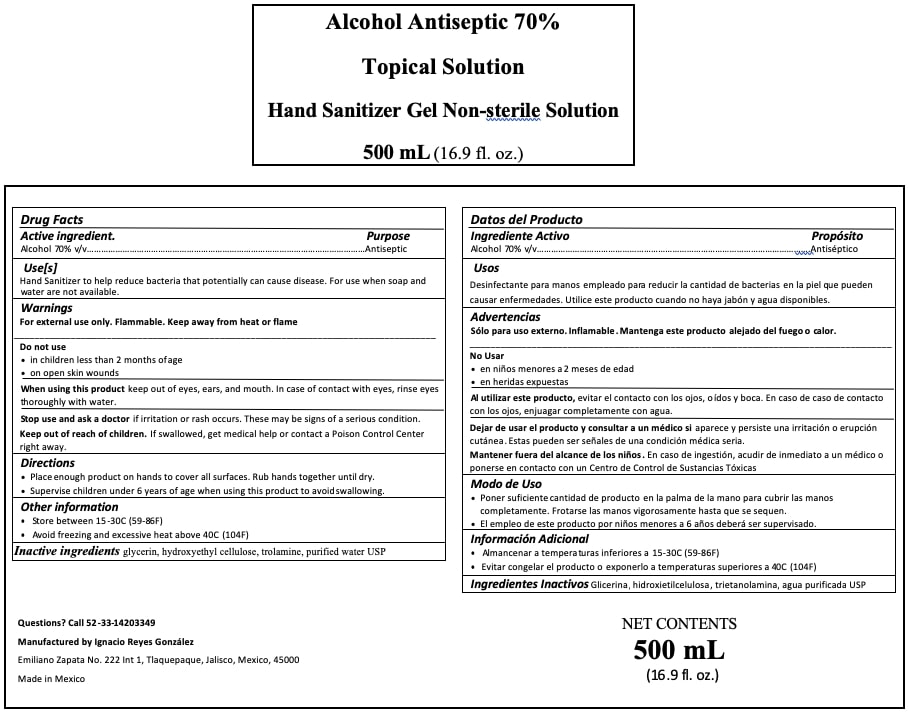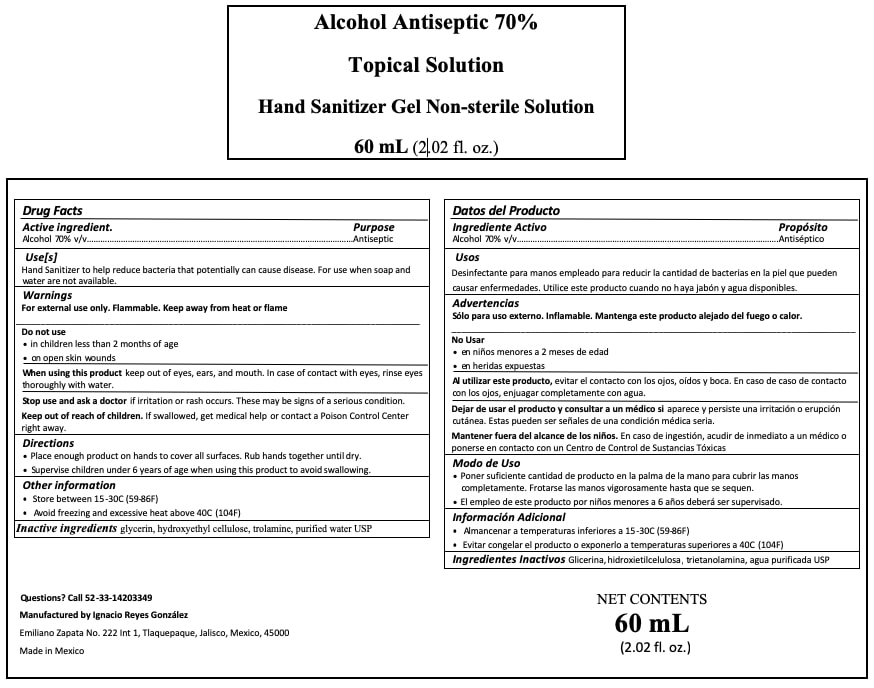 DRUG LABEL: Hand Sanitizer
NDC: 77196-002 | Form: GEL
Manufacturer: Ignacio Reyes González
Category: otc | Type: HUMAN OTC DRUG LABEL
Date: 20200526

ACTIVE INGREDIENTS: ALCOHOL 70 mL/100 mL
INACTIVE INGREDIENTS: GLYCERIN 0.52 mL/100 mL; HYDROXYETHYL CELLULOSE (4000 MPA.S AT 1%) 0.86 mL/100 mL; WATER; TROLAMINE 0.12 mL/100 mL

Hand Sanitizer

The hand sanitizer is manufactured using only the following United States Pharmacopoeia (USP) grade ingredients in the preparation of the product (percentage in final product formulation) consistent with World Health Organization (WHO) recommendations:

1. Alcohol (ethanol) (USP or Food Chemical Codex (FCC) grade) (70%, volume/volume (v/v)) in an Gel solution denatured according to Alcohol and Tobacco Tax and Trade Bureau regulations in 27 CFR part 20.
2. Glycerol (0.52% v/v).
3. Hydroxyethyl Cellulose (0.86% v/v).
4. Trolamine (0.12% v/v).
5. Sterile distilled water or boiled cold water.

Active Ingredient(s)

Alcohol 70% v/v. Purpose: Antiseptic

Purpose

Antiseptic, Hand Sanitizer

Use

Hand Sanitizer to help reduce bacteria that potentially can cause disease. For use when soap and water are not available.

Warnings

For external use only. Flammable. Keep away from heat or flame

Do not use

- in children less than 2 months of age
- on open skin wounds

When using this product keep out of eyes, ears, and mouth. In case of contact with eyes, rinse eyes thoroughly with water.
Stop use and ask a doctor if irritation or rash occurs. These may be signs of a serious condition.
Keep out of reach of children. If swallowed, get medical help or contact a Poison Control Center right away.

Stop use and ask a doctor if irritation or rash occurs. These may be signs of a serious condition.

Keep out of reach of children. If swallowed, get medical help or contact a Poison Control Center right away.

Directions

- Place enough product on hands to cover all surfaces. Rub hands together until dry.
- Supervise children under 6 years of age when using this product to avoid swallowing.

Other information

- Store between 15-30C (59-86F)
- Avoid freezing and excessive heat above 40C (104F)

Inactive ingredients

glycerin, hydroxyethyl cellulose, trolamine, purified water USP

Package Label - Principal Display Panel

200000 mL NDC: 77196-002-02

1000 mL NDC: 77196-002-05

500 mL NDC: 77196-002-06

250 mL NDC: 77196-002-07

110 mL NDC: 77196-002-08

20000 mL NDC: 77196-002-03

1000000 mL NDC: 77196-002-01

220 mL NDC: 77196-002-09

60 mL NDC: 77196-002-10

4000 mL NDC: 77196-002-04